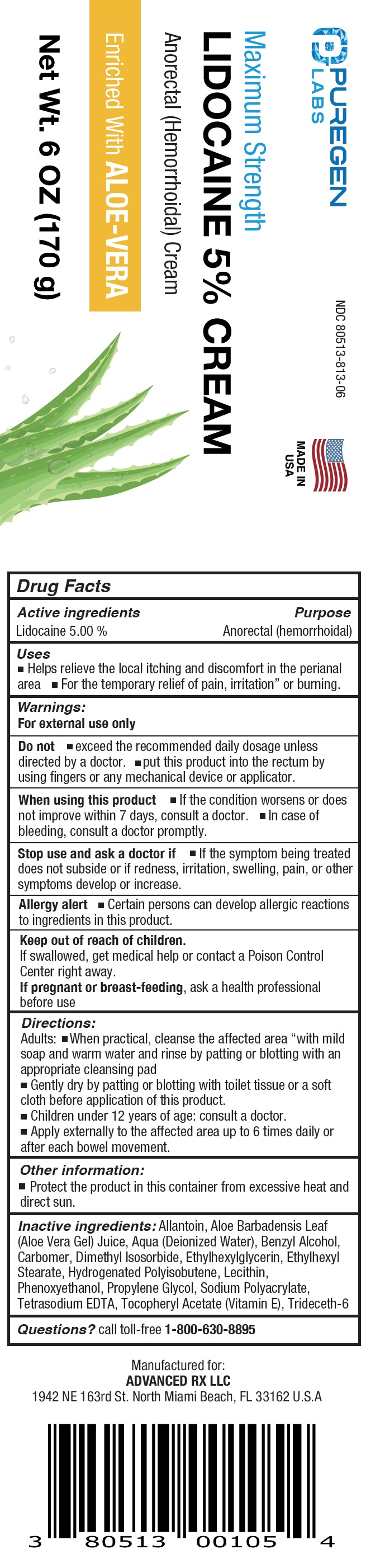 DRUG LABEL: PUREGEN LABS Maximum Strength Lidocaine
NDC: 80513-813 | Form: CREAM
Manufacturer: Advanced Rx LLC
Category: otc | Type: HUMAN OTC DRUG LABEL
Date: 20240411

ACTIVE INGREDIENTS: LIDOCAINE 50 mg/1 g
INACTIVE INGREDIENTS: ALLANTOIN; ALOE VERA LEAF; WATER; BENZYL ALCOHOL; CARBOMER HOMOPOLYMER, UNSPECIFIED TYPE; DIMETHYL ISOSORBIDE; ETHYLHEXYLGLYCERIN; ETHYLHEXYL STEARATE; PHENOXYETHANOL; PROPYLENE GLYCOL; EDETATE SODIUM; .ALPHA.-TOCOPHEROL ACETATE; TRIDECETH-6

PUREGEN LABS Maximum Strength Lidocaine 5% Cream

Active ingredients

Lidocaine 5.00 %

Purpose

Anorectal (hemorrhoidal)

Uses

- Helps relieve the local itching and discomfort in the perianal area
- For the temporary relief of pain, irritation” or burning.

Warnings:

For external use only

Do not

- exceed the recommended daily dosage unless directed by a doctor.
- put this product into the rectum by using fingers or any mechanical device or applicator.

When using this product

- If the condition worsens or does not improve within 7 days, consult a doctor.
- In case of bleeding, consult a doctor promptly.

Stop use and ask a doctor if

- If the symptom being treated does not subside or if redness, irritation, swelling, pain, or other symptoms develop or increase.

Allergy alert

- Certain persons can develop allergic reactions to ingredients in this product.

Keep out of reach of children.

If swallowed, get medical help or contact a Poison Control Center right away.

If pregnant or breast-feeding,

ask a health professional before use

Directions:

Adults:

- When practical, cleanse the affected area “with mild soap and warm water and rinse by patting or blotting with an appropriate cleansing pad
- Gently dry by patting or blotting with toilet tissue or a soft cloth before application of this product.
- Children under 12 years of age: consult a doctor.
- Apply externally to the affected area up to 6 times daily or after each bowel movement.

Other information:

- Protect the product in this container from excessive heat and direct sun.

Inactive ingredients:

Allantoin, Aloe Barbadensis Leaf (Aloe Vera Gel) Juice, Aqua (Deionized Water), Benzyl Alcohol, Carbomer, Dimethyl Isosorbide, Ethylhexylglycerin, Ethylhexyl Stearate, Hydrogenated Polyisobutene, Lecithin, Phenoxyethanol, Propylene Glycol, Sodium Polyacrylate, Tetrasodium EDTA, Tocopheryl Acetate (Vitamin E), Trideceth-6

Questions?

call toll-free 1-800-630-8895